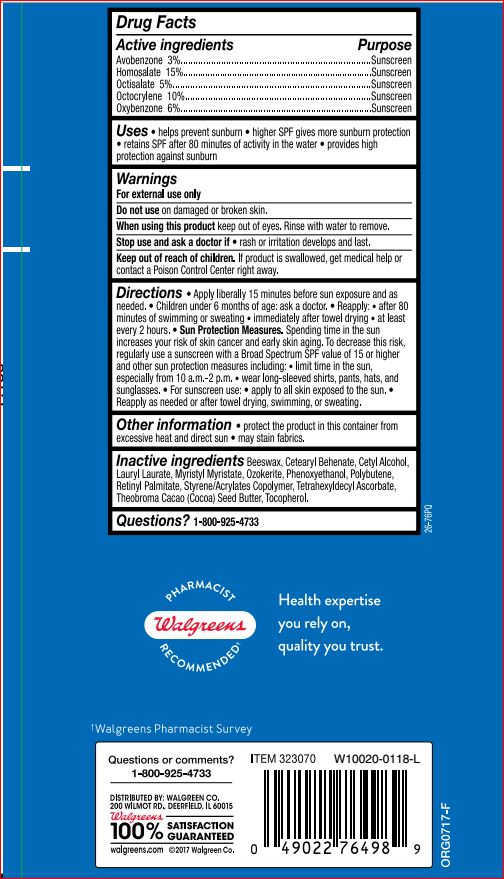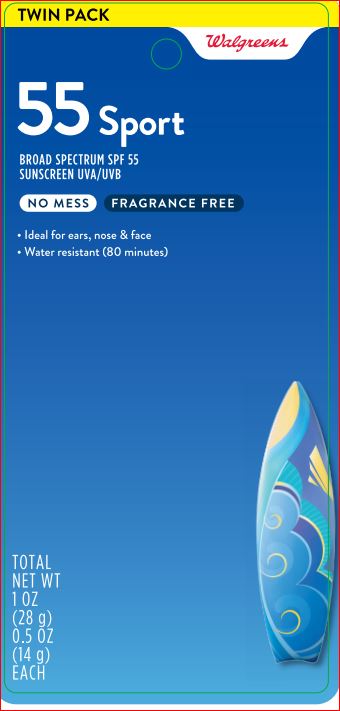 DRUG LABEL: SPF 55 Sport Sunstick
NDC: 0363-3215 | Form: STICK
Manufacturer: Walgreens
Category: otc | Type: HUMAN OTC DRUG LABEL
Date: 20180213

ACTIVE INGREDIENTS: Avobenzone 3 g/100 g; Homosalate 15 g/100 g; Octocrylene 10 g/100 g; Octisalate 5 g/100 g; Oxybenzone 6 g/100 g
INACTIVE INGREDIENTS: CETEARYL BEHENATE; YELLOW WAX; Cetyl Alcohol; Lauryl Laurate; Myristyl Myristate; Phenoxyethanol; POLYBUTENE (1400 MW); VITAMIN A PALMITATE; Tetrahexyldecyl Ascorbate; COCOA BUTTER; Tocopherol; BUTYL METHACRYLATE/METHYL METHACRYLATE/METHACRYLIC ACID/STYRENE CROSSPOLYMER

Drug Facts

Active ingredients Purpose

Avobenzone - 3.0% Sunscreen
Homosalate - 15.0% Sunscreen
Octisalate - 5.0% Sunscreen
Octocrylene - 10.0% Sunscreen
Oxybenzone - 6.0% Sunscreen

INDICATIONS AND USAGE

Uses •Helps prevent sunburn

Warnings:For external use only.

Do not use on damaged or broken skin

When using this product keep out of eye. Rinse with water to remove.

Stop use and ask a doctor if rash occurs

KEEP OUT OF REACH OF CHILDREN

Keep out of reach of the children. If swallowed, get medical help or contact a Poison Control Center right away

Directions

• apply liberally 15 minutes before sun exposure
• reapply:
- After 80 minutes of swimming or sweating
- Immediately after towel drying
- At least every 2 hours
• Sun Protection Measures. Spending time in the sun increases your risk of skin cancer and early skin aging. To decrease this risk, regularly use a sunscreen SPF of 15 or higher and other sun protection measures including:
- Limit time in the sun, especially from 10 a.m. – 2 p.m.
- Wear long sleeve shirts, pants, hats, and sunglasses
• Children under 6 month: Ask a doctor

Inactive ingredients

Beeswax, Cetearyl Behenate, Cetyl Alcohol, Lauryl Laurate, Myristyl Myristate, Ozokerite, Phenoxyethanol, Polybutene, Retinyl Palmitate,
Styrene/Acrylates Copolymer, Tetrahexyldecyl Ascorbate, Theobroma Cacao (Cocoa) Seed Butter, Tocopherol